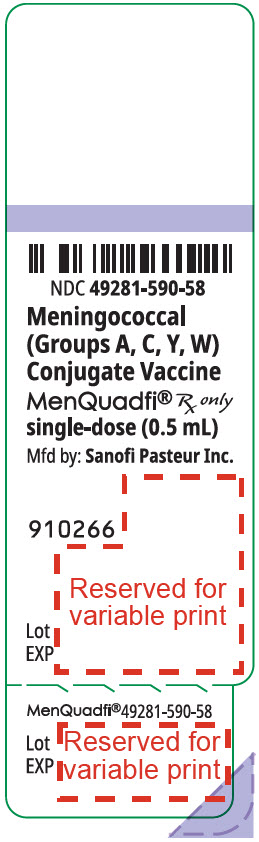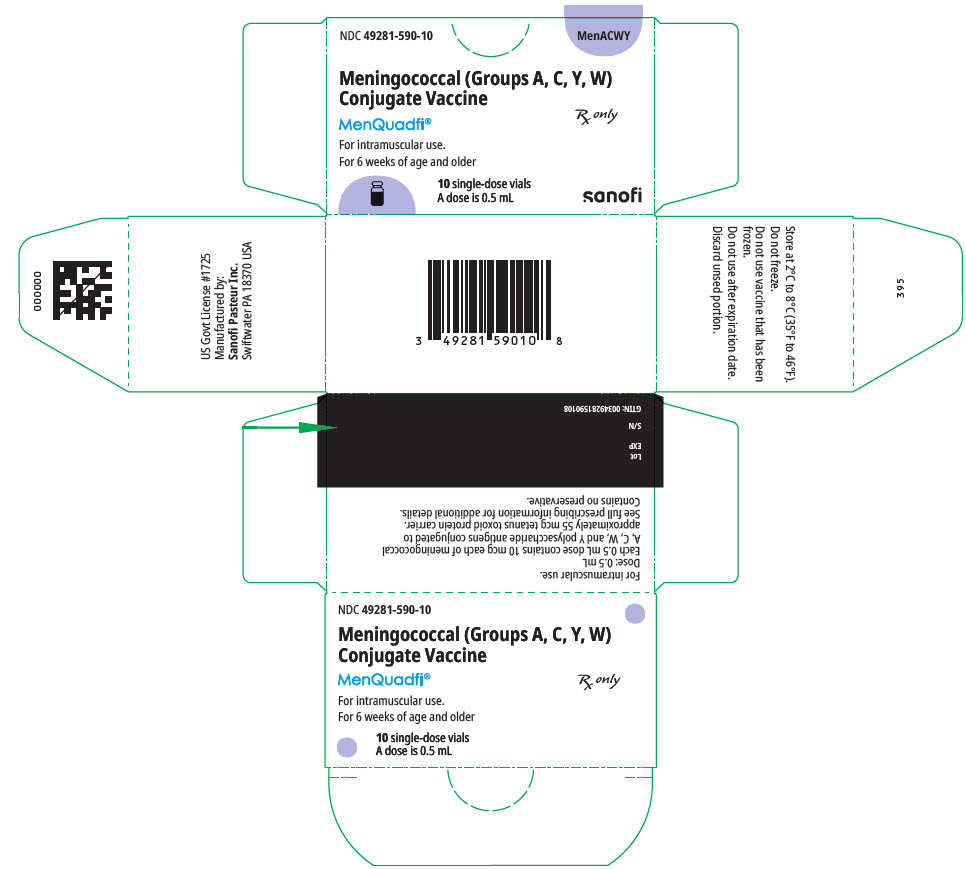 DRUG LABEL: MenQuadfi
NDC: 49281-590 | Form: INJECTION, SOLUTION
Manufacturer: Sanofi Vaccines US Inc.
Category: other | Type: VACCINE LABEL
Date: 20260219

ACTIVE INGREDIENTS: NEISSERIA MENINGITIDIS GROUP A CAPSULAR POLYSACCHARIDE TETANUS TOXOID CONJUGATE ANTIGEN 10 ug/0.5 mL; NEISSERIA MENINGITIDIS GROUP C CAPSULAR POLYSACCHARIDE TETANUS TOXOID CONJUGATE ANTIGEN 10 ug/0.5 mL; NEISSERIA MENINGITIDIS GROUP Y CAPSULAR POLYSACCHARIDE TETANUS TOXOID CONJUGATE ANTIGEN 10 ug/0.5 mL; NEISSERIA MENINGITIDIS GROUP W-135 CAPSULAR POLYSACCHARIDE TETANUS TOXOID CONJUGATE ANTIGEN 10 ug/0.5 mL
INACTIVE INGREDIENTS: SODIUM CHLORIDE 3.35 mg/0.5 mL; SODIUM ACETATE ANHYDROUS 1.23 mg/0.5 mL; WATER

HIGHLIGHTS OF PRESCRIBING INFORMATION

These highlights do not include all the information needed to use MENQUADFI® safely and effectively. See full prescribing information for MENQUADFI.
MenQuadfi, Meningococcal (Groups A, C, Y, W) Conjugate Vaccine
injection, for intramuscular use
Initial U.S. Approval: 2020

RECENT MAJOR CHANGES

Indications and Usage (1) | 5/2025
Dosage and Administration, Dose and Schedule (2.2) | 5/2025

1 INDICATIONS AND USAGE

MenQuadfi is a vaccine indicated for active immunization for the prevention of invasive meningococcal disease caused by Neisseria meningitidis serogroups A, C, W, and Y. MenQuadfi is approved for use in individuals 6 weeks of age and older. (1)

MenQuadfi does not prevent N. meningitidis serogroup B disease. (1)

2 DOSAGE AND ADMINISTRATION

0.5 mL dose for intramuscular use. (2)

Primary Vaccination

- Infants aged from 6 weeks: 4-dose series administered at 2, 4, 6, and 12 through 18 months of age. The first dose may be given as early as 6 weeks of age. (2.2)
- Infants aged 6 months through 11 months: 2-dose series with the second dose administered in the second year of life and at least 3 months after the first dose. (2.2)
- Infants aged 12 months through 23 months: 2-dose series with the second dose administered at least 3 months after the first dose. (2.2)
- Individuals 2 years of age and older: A single dose. (2.2)

Booster Vaccination

- A single dose of MenQuadfi may be administered to individuals 13 years of age and older who are at continued risk for meningococcal disease if at least 3 years have elapsed since a prior dose of meningococcal (groups A, C, W, Y) conjugate vaccine. (2.2)

Vaccination Following Prior Dose of Meningococcal Polysaccharide Vaccine

- A single dose of MenQuadfi may be administered if at least 3 years have elapsed since a prior dose of meningococcal polysaccharide vaccine. (2.2)

3 DOSAGE FORMS AND STRENGTHS

MenQuadfi is an injection. A single dose is 0.5 mL. (3)

4 CONTRAINDICATIONS

Severe allergic reaction to any component of the vaccine, or after a previous dose of MenQuadfi or any other tetanus toxoid-containing vaccine. (4)

6 ADVERSE REACTIONS

Most commonly reported adverse reactions (≥10%) were as follows:

- Infants 6 weeks through 23 months of age:
  - 4-dose series given at 2, 4, 6, and 12 through 18 months of age: tenderness (38.5%–45.6%), erythema (12.5%–19.5%), and swelling (9.6%–12.7%) at the injection site; irritability (40.1%–51.9%), crying abnormal (27.3%–42.1%), drowsiness (25.1%–43.4%), appetite lost (17.3%–21.8%), fever (7.8%–17.6%), vomiting (3.5%–13.2%). (6)
  - 2-dose series given at 6 through 7 months and 12 through 13 months of age: tenderness (30.1%–42.7%), erythema (21.1%–21.8%), and swelling (14.5%–16.0%) at the injection site; irritability (40.0%–49.0%), crying abnormal (26.6%–35.0%), drowsiness (27.7%–36.5%), appetite lost (15.2%–17.1%), fever (9.3%–12.9%), vomiting (5.5%–8.5%). (6)
- Children 2 through 9 years of age: pain (38.6%), erythema (22.6%), and swelling (13.8%) at the injection site; malaise (21.1%), myalgia (20.1%), and headache (12.5%). (6)
- Adolescents aged 10 through 17 years of age: injection site pain (34.8%–45.2%), myalgia (27.4%–35.3%), headache (26.5%–30.2%), and malaise (19.4%–26.0%). (6)
- Adults aged 18 through 55 years: injection site pain (41.9%), myalgia (35.6%), headache (29.0%), and malaise (22.9%). (6)
- Adults 56 years of age and older: pain at the injection site (25.5%), myalgia (21.9%), headache (19.0%), and malaise (14.5%). (6)

In adolescents and adults, rates of solicited adverse reactions following a booster dose were comparable to those observed following primary vaccination. (6)

To report SUSPECTED ADVERSE REACTIONS, contact Sanofi Pasteur Inc., Discovery Drive, Swiftwater, PA 18370 at 1-800-822-2463 (1-800-VACCINE) or VAERS at 1-800-822-7967 or www.vaers.hhs.gov.

FULL PRESCRIBING INFORMATION

1 INDICATIONS AND USAGE

MenQuadfi® is a vaccine indicated for active immunization for the prevention of invasive meningococcal disease caused by Neisseria meningitidis serogroups A, C, W, and Y. MenQuadfi is approved for use in individuals 6 weeks of age and older.

MenQuadfi does not prevent N. meningitidis serogroup B disease.

2 DOSAGE AND ADMINISTRATION

2.1 Preparation for Administration

MenQuadfi is a clear, colorless solution.

Parenteral drug products should be inspected visually for particulate matter and discoloration prior to administration, whenever solution and container permit. If any of these conditions exist, the vaccine should not be administered.

2.2 Dose and Schedule

Administer MenQuadfi as a single 0.5 mL injection intramuscularly.

Primary Vaccination:

Table 1: Dosing Schedule for MenQuadfi Primary Vaccination
Age at First Dose | Primary Vaccination Schedule
2 months | 4-dose series at 2, 4, 6, and 12 through 18 months of age. The first dose may be given as early as 6 weeks.
6 months through 11 months | 2-dose series with the second dose administered in the second year of life and at least 3 months after the first dose.
12 months through 23 months | 2-dose series with the second dose administered at least 3 months after the first dose.
2 years and older | A single dose

Booster Vaccination

- A single dose of MenQuadfi may be administered to individuals 13 years of age and older who are at continued risk for meningococcal disease if at least 3 years have elapsed since a prior dose of meningococcal (groups A, C, W, Y) conjugate vaccine.

Vaccination Following Prior Dose of Meningococcal Polysaccharide Vaccine

- A single dose of MenQuadfi may be administered if at least 3 years have elapsed since a prior dose of meningococcal polysaccharide vaccine.

3 DOSAGE FORMS AND STRENGTHS

MenQuadfi is an injection. A single dose is 0.5 mL.

4 CONTRAINDICATIONS

Severe allergic reaction to any component of the vaccine, or after a previous dose of MenQuadfi or any other tetanus toxoid-containing vaccine [see Description (11)].

5 WARNINGS AND PRECAUTIONS

5.1 Management of Acute Allergic Reactions

Appropriate medical treatment must be immediately available to manage potential anaphylactic reactions following administration of MenQuadfi.

5.2 Altered Immunocompetence

Reduced Immune Response

Some individuals with altered immunocompetence, including some individuals receiving immunosuppressant therapy, may have reduced immune responses to MenQuadfi.

Complement Deficiency

Persons with certain complement deficiencies and persons receiving treatment that inhibits terminal complement activation (for example, eculizumab) are at increased risk for invasive disease caused by N. meningitidis, including invasive disease caused by serogroups A, C, W, and Y, even if they develop antibodies following vaccination with MenQuadfi [see Clinical Pharmacology (12.1)].

5.3 Syncope

Syncope (fainting) may occur in association with administration of injectable vaccines, including MenQuadfi. Procedures should be in place to avoid injury from fainting.

5.4 Guillain-Barré Syndrome

Guillain-Barré syndrome (GBS) has been reported in temporal relationship following administration of another U.S.-licensed meningococcal quadrivalent polysaccharide conjugate vaccine. The decision by the healthcare professional to administer MenQuadfi to persons with a history of GBS should take into account the expected benefits and potential risks.

5.5 Tetanus Immunization

Immunization with MenQuadfi does not substitute for routine tetanus immunization.

5.6 Limitations of Vaccine Effectiveness

Vaccination with MenQuadfi may not protect all vaccine recipients.

6 ADVERSE REACTIONS

6.1 Clinical Trials Experience

Because clinical trials are conducted under widely varying conditions, adverse reaction rates observed in the clinical trial(s) of a vaccine cannot be directly compared to rates in the clinical trial(s) of another vaccine and may not reflect the rates observed in practice.

The safety of MenQuadfi in individuals 6 weeks of age and older was evaluated in ten randomized, active-controlled, multi-center clinical studies conducted in the U.S. and Puerto Rico. A total of 4273 participants younger than 2 years of age received at least one dose of either a 4-dose series (N=3807) or a 2-dose series (N=466) of MenQuadfi and were included in the safety analyses. In studies that enrolled participants 2 years of age and older, a total of 5787 participants received a single dose, either as a primary dose (N=4517), a booster dose (N=1119) of MenQuadfi following priming with a meningococcal conjugate vaccine, or a dose of MenQuadfi following a prior dose of meningococcal polysaccharide vaccine (N=151) and were included in the safety analyses.

Safety Monitoring

Participants were monitored for immediate reactions for 30 minutes following each vaccination while at the study site. Solicited injection site and systemic reactions were recorded by participants or by parents/guardians in a diary card at home daily for 7 days following vaccination. At subsequent visits approximately 1 to 2 months post-vaccination, participants or parents/guardians reviewed diary cards with study investigators and when necessary, made corrections or clarifications. All unsolicited adverse events that occurred within 30 days following vaccination were recorded by participants or by parents/guardians, then collected and reported by the investigator. Unsolicited adverse events that were medically attended (i.e., visits to an emergency room, or an unexpected visit to a health care provider), and all serious adverse events (SAEs) were collected for at least 6 months after vaccination for all studies except Study 10 [NCT04142242], in which these safety data were collected for at least 1 month.

Primary Vaccination

Infants 6 weeks through 23 months of age

The safety of MenQuadfi in infants aged 6 weeks through 23 months of age who received at least one dose and up to 4 doses of MenQuadfi was evaluated in three clinical studies.

4-Dose Series (infants initiating vaccination at 2 months of age):

The safety of MenQuadfi in infants from 6 weeks of age vaccinated with a 4-dose series (at 2, 4, 6, and 12 through 18 months) was evaluated in Study 1 (NCT03537508). The safety analysis set included 1727 participants who received at least one dose of MenQuadfi (1375 participants received a full 4-dose series) and 867 participants received at least one dose of Menveo® [Meningococcal (Groups A, C, Y, and W-135) Oligosaccharide Diphtheria CRM197 Conjugate Vaccine] (705 participants received a full 4-dose series). Each of these vaccines was administered concomitantly with U.S. licensed vaccines including Pentacel® (diphtheria, tetanus, acellular pertussis, inactivated polio and Haemophilus influenzae type b vaccine [DTaP-IPV/Hib]) given at 2, 4, 6, and at 15 through 18 months of age; Prevnar 13® (pneumococcal 13-valent conjugate vaccine [PCV13]) given at 2, 4, 6, and 12 months of age; RotaTeq® (rotavirus vaccine) given at 2, 4, and 6 months of age; Engerix-B® (hepatitis B vaccine [HepB]) given at 2 and 6 months of age (first dose given 28 days prior to study); M-M-R II® (measles, mumps, and rubella vaccine [MMR]) and Varivax® (varicella vaccine) given at 12 months of age; and Havrix® (hepatitis A vaccine [HepA]) given at 15 through 18 months of age. Of the participants who received MenQuadfi (N=1727), 47.2% were female, 81.9% were White, 11.8% were Black or African American, 0.8% were Asian, 4.4% were of other racial groups, and 48.1% were of Hispanic or Latino ethnicity. There were no substantive differences in demographic characteristics between vaccine groups.

Among participants in Study 1 who received at least one dose of MenQuadfi, 133 (7.7%) were born preterm (31 to < 37 weeks of gestational age); of these 133 preterm infants, 121 were born 34 to < 37 weeks of gestation. Among participants who received at least one dose of Menveo, 58 (6.7%) were born preterm; of these 58 preterm infants, 47 were born 34 to < 37 weeks of gestation. There were no notable differences in the rates and severity of adverse reactions between preterm and full-term infants after any vaccination.

The rates and severity of the solicited adverse reactions that occurred within 7 days following each dose of MenQuadfi and comparator vaccines are presented in Table 2.

Table 2: Percentages of Solicited Injection-Site Reactions and Systemic Adverse Reactions within 7 Days after Each Vaccination with MenQuadfi with Concomitantly Administered Vaccines or Comparator Vaccines Administered at 2, 4, 6, and 12 through 18 Months of Age (Study 1) [Clinical trial identifier NCT03537508. Pentacel was given at 2, 4, 6, and at 15 through 18 months of age; Prevnar 13 was given at 2, 4, 6, and 12 months of age; RotaTeq was given at 2, 4, and 6 months of age; Engerix- B was given at 2 and 6 months of age (first dose given 28 days prior to study); M-M-R II and Varivax was given at 12 months of age; and Havrix was given at 15 through 18 months of age.]
 | Dose 1 |  | Dose 2 |  | Dose 3 |  | Dose 4
 | MenQuadfi N [N is the number of vaccinated participants with available data for the events listed] =1552–1625 % | Menveo N=789–824 % | MenQuadfi N=1456–1519 % | Menveo N=743–786 % | MenQuadfi N=1391–1458 % | Menveo N=701–748 % | MenQuadfi (12 through 15 months) [There was an overlap in 15 to < 16 month old participants included in both groups (MenQuadfi [12 through 15 months] and MenQuadfi [15 through 18 months]). There were 21/938 (2.2%) participants aged 15 to < 16 months included in the MenQuadfi (12 through 15 months) group and 320/444 (72.1%) participants aged 15 to < 16 months in the MenQuadfi (15 through 18 months) group.] N=798–864 % | Menveo (12 months) N=419–438 % | MenQuadfi (15 through 18 months) N=383–401 % | Pentacel and Havrix without MenACWY (15 through 18 months) N=184–199 %
 | MenQuadfi N [N is the number of vaccinated participants with available data for the events listed] =1552–1625 % | Menveo N=789–824 % | MenQuadfi N=1456–1519 % | Menveo N=743–786 % | MenQuadfi N=1391–1458 % | Menveo N=701–748 % | MenQuadfi (12 through 15 months) [There was an overlap in 15 to < 16 month old participants included in both groups (MenQuadfi [12 through 15 months] and MenQuadfi [15 through 18 months]). There were 21/938 (2.2%) participants aged 15 to < 16 months included in the MenQuadfi (12 through 15 months) group and 320/444 (72.1%) participants aged 15 to < 16 months in the MenQuadfi (15 through 18 months) group.] N=798–864 % | Menveo (12 months) N=419–438 % | MenQuadfi (15 through 18 months) N=383–401 % | Pentacel | Havrix
Local Reactions
Injection Site Tenderness [Any: Minor reaction when injection site is touched; Grade 3: Cries when injected limb is mobilized, or the movement of the injected limb is reduced] | 45.6 | 43.3 | 43.6 | 43.9 | 42.4 | 40.6 | 38.5 | 40.6 | 40.8 | 39.7 | 37.7
Grade 3 | 4.4 | 3.4 | 3.4 | 3.3 | 3.2 | 2.4 | 2.2 | 2.3 | 1.8 | 3.0 | 2.0
Injection Site Erythema [Any: > 0 mm; Grade 3: ≥ 50 mm] | 12.5 | 11.4 | 18.3 | 16.3 | 19.5 | 19.7 | 16.2 | 20.6 | 18.7 | 16.1 | 12.1
Grade 3 | 0 | 0.1 | 0 | 0.3 | 0 | 0.1 | 0.1 | 0 | 0.5 | 1.0 | 0.5
Injection Site Swelling | 9.6 | 9.0 | 12.3 | 10.1 | 12.7 | 13.0 | 10.2 | 15.1 | 12.3 | 14.6 | 11.1
Grade 3 | < 0.1 | 0 | < 0.1 | 0.3 | 0 | 0.1 | 0.1 | 0 | 0 | 1.0 | 0.5
Systemic Reactions
Fever [Any: ≥ 100.4°F (38.0°C); Grade 3: ≥ 103.1°F (39.5°C)] | 7.8 | 6.6 | 17.6 | 17.9 | 15.2 | 16.5 | 14.8 | 14.3 | 11.0 | 8.2
Grade 3 | < 0.1 | 0 | 0.6 | 0.8 | 0.7 | 0.3 | 0.5 | 1.2 | 1.0 | 0.5
Vomiting [Any: 1 episode per 24 hours; Grade 3: ≥ 6 episodes per 24 hours or requiring parenteral hydration] | 13.2 | 10.9 | 9.7 | 8.5 | 9.5 | 6.7 | 4.6 | 5.7 | 3.5 | 2.0
Grade 3 | 0.5 | 0.2 | 0.3 | 0.5 | 0.3 | 0.5 | 0.1 | 0.2 | 0.3 | 0
Crying abnormal [Any: < 1 hour; Grade 3: > 3 hours] | 40.9 | 39.4 | 42.1 | 41.5 | 37.6 | 36.6 | 32.1 | 35.2 | 27.3 | 27.3
Grade 3 | 2.8 | 2.3 | 3.6 | 2.8 | 3.0 | 1.7 | 2.9 | 2.5 | 1.3 | 2.0
Drowsiness [Any: Sleepier than usual/less interested in surroundings; Grade 3: Sleeping most of the time or difficult to wake up] | 43.4 | 42.3 | 38.2 | 38.8 | 35.3 | 34.5 | 33.6 | 34.2 | 25.1 | 25.3
Grade 3 | 2.5 | 2.7 | 1.9 | 2.4 | 2.0 | 2.1 | 2.2 | 1.1 | 1.0 | 2.0
Appetite lost [Any: Eating less than normal; Grade 3: Refuses ≥ 3 feeds / meals or refuses most feeds / meals] | 20.5 | 20.4 | 19.9 | 22.9 | 18.9 | 19.0 | 21.8 | 21.5 | 17.3 | 17.7
Grade 3 | 0.9 | 0.7 | 0.6 | 0.9 | 1.0 | 0.8 | 0.9 | 2.1 | 0.8 | 1.5
Irritability [Any: Easily consolable; Grade 3: Inconsolable] | 51.9 | 51.0 | 51.4 | 50.9 | 47.4 | 46.3 | 46.9 | 47.0 | 40.1 | 38.9
Grade 3 | 3.9 | 2.8 | 4.7 | 5.2 | 4.3 | 2.7 | 4.2 | 3.0 | 2.0 | 4.0

The safety of MenQuadfi in infants from 6 weeks of age vaccinated with a 4-dose series (at 2, 4, 6, and 12 months) was evaluated in Study 2 (NCT03673462). The safety analysis set included 2080 participants who received at least one dose of MenQuadfi (1836 participants received a full 4-dose series) and 697 participants received at least one dose of Menveo (622 participants received a full 4-dose series). Each of these vaccines was administered concomitantly with U.S. licensed vaccines including Pentacel (DTaP-IPV/Hib) given at 2, 4, and 6 months of age; Prevnar 13 (PCV13) given at 2, 4, 6, and 12 months of age; RotaTeq (rotavirus vaccine) given at 2, 4, and 6 months of age; Engerix-B (HepB) given at 2 and 6 months of age (first dose given 28 days prior to study); M-M-R II (MMR) and Varivax (varicella vaccine) given at 12 months of age. Of the participants who received MenQuadfi (N=2080), 47.7% were female, 81.9% were White, 10.1% were Black or African American, 1.3% were Asian, 5.7% were of other racial groups, and 26.8% were of Hispanic or Latino ethnicity. There were no substantive differences in demographic characteristics between vaccine groups.

Among participants in Study 2 who received at least one dose of MenQuadfi, 89 (4.3%) were born preterm (31 to < 37 weeks of gestational age); of these 89 preterm infants, 83 were born 34 to < 37 weeks of gestation. Among participants who received at least one dose of Menveo, 20 (2.9%) were born preterm at 34 to < 37 weeks of gestation. There were no notable differences in the rates and severity of adverse reactions between preterm and full-term infants after any vaccination.

In Study 1 and Study 2, following any dose in the 4-dose series, SAEs were reported by 5.3% of participants following MenQuadfi and 3.6% of participants following Menveo during the entire study period (which includes the first study vaccination through 6 months after the final vaccination). SAEs were reported by 0.6% of participants following MenQuadfi and 0.3% of participants reported SAEs following Menveo within 7 days after vaccination. SAEs were reported by 2.2% of participants following MenQuadfi and 1.2% of participants following Menveo within 30 days after vaccination.

There were two SAEs of febrile seizure considered possibly related to vaccination with MenQuadfi following the fourth dose when concomitantly administered with MMR, varicella, and PCV13 vaccines at 12 months of age (Study 2). One case occurred one day post vaccination. The other case occurred 9 days post vaccination. Neither febrile seizure was reported as prolonged, and neither study participant reported a recurrent febrile seizure through 6 months after the last dose of MenQuadfi.

2-Dose Series (infants initiating vaccination at 6 months through 23 months of age):

The safety of MenQuadfi in infants from 6 months of age vaccinated with a 2-dose series (at 6 through 7 months and 12 through 13 months) was evaluated in Study 3 (NCT03691610). The safety analysis set included 370 participants who received at least one dose of MenQuadfi (309 participants received a full 2-dose series) and 361 participants who received at least one dose of Menveo (302 participants received a full 2-dose series). Each of these vaccines was administered concomitantly with U.S. licensed vaccines including Pentacel (DTaP-IPV/Hib) or Pediarix® (DTaP-IPV-HepB), ActHIB® or Hiberix® or PedvaxHIB® (Hib vaccine), RotaTeq (rotavirus vaccine), and Engerix-B (HepB) given at 6 months of age; Prevnar 13 (PCV13) given at 6 and 13 months of age; and M-M-R II (MMR) and Varivax (varicella vaccine) given at 12 months of age. Of the participants who received MenQuadfi (N=370), 47.6% were female, 74.1% were White, 17% were Black or African American, 1.6% were Asian, 7.3% were of other racial groups, and 45.1% were of Hispanic or Latino ethnicity. There were no substantive differences in demographic characteristics between the vaccine groups.

The rates and severity of the solicited adverse reactions that occurred within 7 days following MenQuadfi compared with Menveo (Study 3) are presented in Table 3.

Table 3: Percentages of Solicited Injection-Site Reactions and Systemic Adverse Reactions within 7 Days after Each Vaccination with MenQuadfi or Menveo, with Concomitantly Administered Vaccines, in a 2-dose Series with the First Dose Administered at 6 through 7 Months of Age and the Second Dose Administered 12 through 13 Months of age (Study 3) [Clinical trial identifier NCT03691610. At 6 months. Pediarix and a Hib vaccine (ActHIB or Hiberix or PedvaxHIB) OR Pentacel were given along with Prevnar 13, RotaTeq and Engerix-B. At 12 months of age, M-M-R II and Varivax were given.]
 | Dose 1 |  |  |  | Dose 2
 | MenQuadfi N [N is the number of vaccinated participants with available data for the events listed] =341–351 % |  | Menveo N=325–339 % |  | MenQuadfi N=279–290 % |  | Menveo N=261–273 %
Adverse Reactions | Any | Grade 3 | Any | Grade 3 | Any | Grade 3 | Any | Grade 3
Local Reactions
Injection Site Tenderness [Any: Minor reaction when injection site is touched; Grade 3: Cries when injected limb is mobilized, or the movement of the injected limb is reduced] | 42.7 | 2.3 | 34.7 | 2.1 | 30.1 | 0.7 | 32.0 | 1.5
Injection Site Erythema | 21.1 | 0.0 | 21.6 | 0.0 | 21.8 | 0.0 | 21.7 | 0.7
Injection Site Swelling [Any: > 0 mm; Grade 3: ≥ 50 mm] | 16.0 | 0.0 | 15.7 | 0.0 | 14.5 | 0.3 | 14.7 | 0.4
Systemic Reactions
Fever [Any: ≥ 100.4°F (38.0°C); Grade 3: ≥ 103.1°F (39.5°C)] | 12.9 | 0.3 | 12.3 | 0.6 | 9.3 | 0.7 | 7.7 | 0.8
Vomiting [Any: 1 episode per 24 hours; Grade 3: ≥ 6 episodes per 24 hours or requiring parenteral hydration] | 8.5 | 0.3 | 8.0 | 0.0 | 5.5 | 0.3 | 3.7 | 0.4
Crying abnormal [Any: < 1 hour; Grade 3: > 3 hours] | 35.0 | 1.7 | 32.4 | 1.2 | 26.6 | 0.7 | 25.3 | 0.7
Drowsiness [Any: Sleepier than usual/less interested in surroundings; Grade 3: Sleeping most of the time or difficult to wake up] | 36.5 | 2.3 | 38.9 | 2.4 | 27.7 | 0.7 | 31.5 | 1.1
Appetite lost [Any: Eating less than normal; Grade 3: Refuses ≥ 3 feeds / meals or refuses most feeds / meals] | 17.1 | 1.4 | 16.2 | 0.6 | 15.2 | 0.7 | 17.3 | 0.7
Irritability [Any: Easily consolable; Grade 3: Inconsolable] | 49.0 | 4.8 | 45.1 | 3.5 | 40.0 | 3.1 | 40.4 | 1.8

Following any dose in the 2-dose series administered at 6 through 7 months and 12 through 13 months of age, SAEs were reported by 1.6% of participants following MenQuadfi and 3.3% of participants following Menveo during the entire study period (which includes the first study vaccination through 6 months after the final vaccination). No SAE were reported within 7 days following MenQuadfi and 0.3% of participants reported an SAE following Menveo. SAEs were reported by 0.3% of participants following MenQuadfi and 0.6% of participants following Menveo within 30 days after vaccination. No SAEs were determined to be vaccine related.

In Study 3, safety was also assessed in 199 participants vaccinated with the 2-dose series at 17 through 19 months and 20 through 23 months of age. The safety analysis set included 96 participants who received at least one dose of MenQuadfi (86 participants received a full 2-dose series) and 103 participants who received at least one dose of Menactra® [Meningococcal (Groups A, C, Y, and W-135) Polysaccharide Diphtheria Toxoid Conjugate Vaccine] (96 participants who received a full 2-dose series). Of the participants who received MenQuadfi (N=96), 50% were female, 82.3% were White, 11.5% were Black or African American, 2.1% were Asian, 4.2% were of other racial groups, and 32.3% were of Hispanic or Latino ethnicity. There were no substantive differences in demographic characteristics between the vaccine groups.

The rates and severity of the solicited adverse reactions that occurred within 7 days following MenQuadfi compared with Menactra (Study 3) are presented in Table 4.

Table 4: Percentages of Solicited Injection-Site Reactions and Systemic Adverse Reactions within 7 Days after Each Vaccination with MenQuadfi or Menactra in a 2-dose Series (first dose administered at 17 through 19 months and second dose at 20 through 23 Months of Age) (Study 3) [Clinical trial identifier NCT03691610]
 | Dose 1 |  |  |  | Dose 2
 | MenQuadfi N [N is the number of vaccinated participants with available data for the events listed] =89–90 % |  | Menactra N=98–99 % |  | MenQuadfi N=82 % |  | Menactra N=91–93 %
Adverse Reactions | Any | Grade 3 | Any | Grade 3 | Any | Grade 3 | Any | Grade 3
Local Reactions
Injection Site Tenderness [Any: Minor reaction when injection site is touched; Grade 3: Cries when injected limb is mobilized, or the movement of the injected limb is reduced] | 34.4 | 0.0 | 35.4 | 1.0 | 41.5 | 0.0 | 26.9 | 1.1
Injection Site Erythema [Any: > 0 mm; Grade 3: ≥ 50 mm] | 22.2 | 0.0 | 22.2 | 0.0 | 25.6 | 0.0 | 16.1 | 0.0
Injection Site Swelling | 18.9 | 0.0 | 12.1 | 0.0 | 20.7 | 0.0 | 7.5 | 0.0
Systemic Reactions
Fever [Any: ≥ 100.4°F (38.0°C); Grade 3: ≥ 103.1°F (39.5°C)] | 11.2 | 1.1 | 12.2 | 1.0 | 11.0 | 0.0 | 8.8 | 0.0
Vomiting [Any: 1 episode per 24 hours; Grade 3: ≥ 6 episodes per 24 hours or requiring parenteral hydration] | 4.4 | 0.0 | 6.1 | 0.0 | 3.7 | 0.0 | 3.2 | 1.1
Crying abnormal [Any: < 1 hour; Grade 3: > 3 hours] | 26.7 | 1.1 | 26.3 | 2.0 | 25.6 | 0.0 | 19.4 | 1.1
Drowsiness [Any: Sleepier than usual/less interested in surroundings; Grade 3: Sleeping most of the time or difficult to wake up] | 24.4 | 0.0 | 23.2 | 2.0 | 23.2 | 0.0 | 14.0 | 1.1
Appetite lost [Any: Eating less than normal; Grade 3: Refuses ≥ 3 feeds / meals or refuses most feeds / meals] | 21.1 | 0.0 | 23.2 | 1.0 | 20.7 | 0.0 | 25.8 | 1.1
Irritability [Any: Easily consolable; Grade 3: Inconsolable] | 40.0 | 3.3 | 43.4 | 3.0 | 35.4 | 1.2 | 33.3 | 3.2

Following any dose in the 2-dose series administered at 17 through 19 months and 20 through 23 months of age, SAEs were reported by 1.0% of participants following MenQuadfi and 3.9% of participants following Menactra during the entire study period (which includes the first study vaccination through 6 months after the final vaccination). No SAEs were reported within 7 or 30 days following MenQuadfi. SAEs were reported by 1.0% of participants within 7 days and 1.9% of participants within 30 days following Menactra. Among participants who received MenQuadfi, no SAEs were determined to be vaccine related.

No notable differences in the rates and severity of solicited adverse reactions were observed following a 2-dose series when initiated at 6 months or 17 months of age.

Children 2 through 9 years of age

The safety of MenQuadfi in children 2 years through 9 years of age was evaluated in Study 4 (NCT03077438). The safety analysis set included 498 participants who received MenQuadfi and 494 participants who received Menveo. Of the participants 2 through 9 years of age who received MenQuadfi (N=498), 50.2% were 2 through 5 years of age, 49.8% were 6 through 9 years of age, 49.0% were female, 80.5% were White, 13.3% were Black or African American, 0.4% were Asian, 5.2% were of other racial groups, and 22.9% were of Hispanic or Latino ethnicity. There were no substantive differences in demographic characteristics between the vaccine groups.

The rates and severity of the solicited adverse reactions that occurred within 7 days following MenQuadfi compared with Menveo (Study 4) are presented in Table 5.

SAEs were reported at a rate of 1.4% following MenQuadfi and at a rate of 0.6% following Menveo during the entire study period. Most SAEs were reported more than 30 days following vaccination and were commonly occurring events in the general population in this age group. No SAEs were determined to be vaccine related.

Table 5: Percentages of Solicited Injection-Site Reactions and Systemic Adverse Reactions within 7 Days after Vaccination with MenQuadfi or Menveo in Children 2 through 9 Years of Age (Study 4) [Clinical trial identifier NCT03077438]
 | MenQuadfi (N [N is the number of vaccinated participants with available data for the events listed] =484–487) % |  | Menveo (N=479–486) %
Adverse Reactions | Any | Grade 3 | Any | Grade 3
Local Reactions
Injection Site Pain [Grade 3: Unable to perform usual activities] | 38.6 | 0.6 | 42.4 | 1.0
Injection Site Erythema [Any: > 0 mm; Grade 3: ≥ 50 mm] | 22.6 | 3.1 | 31.5 | 9.9
Injection Site Swelling | 13.8 | 1.4 | 21.5 | 5.6
Systemic Reactions
Myalgia [Grade 3: Prevents daily activity] | 20.1 | 0.4 | 23.0 | 0.8
Malaise | 21.1 | 1.8 | 20.4 | 1.0
Headache | 12.5 | 0.0 | 11.5 | 0.4
Fever [Any: ≥ 100.4°F (38.0°C); Grade 3: ≥ 102.1°F (39.0°C)] | 1.9 | 0.0 | 2.7 | 0.4

Adolescents 10 through 17 years of age

The safety of MenQuadfi in adolescents 10 through 17 years of age was evaluated in two clinical trial studies Study 5 (NCT02199691) and Study 6 (NCT02842853). The safety analysis set in these two studies included 3,196 participants who received MenQuadfi alone (1,684 participants), MenQuadfi concomitantly with Adacel® [Tetanus Toxoid, Reduced Diphtheria Toxoid and Acellular Pertussis Vaccine, Adsorbed] (Tdap) and Gardasil® [Human Papillomavirus Quadrivalent (Types 6, 11, 16, and 18) Vaccine, Recombinant] (HPV) (392 participants), the concomitant vaccines without MenQuadfi (296 participants), or a U.S.-licensed comparator meningococcal vaccine (824 participants). The comparator meningococcal vaccine was either Menveo (501 participants) or Menactra (323 participants).

Of the participants 10 through 17 years of age who received MenQuadfi (N=1684), 49.6% were female. Among those with reported race and ethnicity, 79.3% were White, 14.2% were Black or African American, 1.1% were Asian, 5.4% were of other racial groups, and 21.5% were of Hispanic or Latino ethnicity. Mean age was 11.9 years at time of administration. There were no substantive differences in demographic characteristics between the vaccine groups.

The rates and severity of the solicited adverse reactions that occurred within 7 days following MenQuadfi compared with Menveo and Menactra are presented in Table 6. The most common injection site and systemic reactions occurring after MenQuadfi administration (in Study 5 and Study 6) were injection site pain (45.2% and 34.8%) and myalgia (35.3% and 27.4%), respectively.

In Study 5, SAEs were reported by 0.8% of participants following MenQuadfi and 0.8% of participants following Menveo. In Study 6, SAEs were reported by 0.3% of participants following MenQuadfi and 0.9% of participants following Menactra. No SAEs were determined to be vaccine related.

Table 6: Percentages of Solicited Injection-Site Reactions and Systemic Adverse Reactions within 7 Days after Vaccination with MenQuadfi or Menveo in Individuals 10 through 17 Years of Age (Study 5) [Clinical trial identifier NCT02199691] and MenQuadfi or Menactra in Individuals 10 through 17 Years of Age (Study 6) [Clinical trial identifier NCT02842853]
 | Study 5 |  |  |  | Study 6
 | MenQuadfi (N [N is the number of vaccinated participants with available data for the events listed] =494–496) % |  | Menveo (N=488–491) % |  | MenQuadfi (N=1129–1159) % |  | Menactra (N=310–314) %
Adverse Reactions | Any | Grade 3 | Any | Grade 3 | Any | Grade 3 | Any | Grade 3
Local Reactions
Injection Site Pain [Grade 3: Prevents daily activity] | 45.2 | 1.4 | 42.5 | 1.0 | 34.8 | 1.8 | 41.4 | 2.2
Injection Site Erythema [Any: > 25 mm; Grade 3: > 100 mm] | 5.0 | 0.4 | 7.5 | 1.2 | 4.5 | 0.3 | 4.5 | 0.3
Injection Site Swelling | 5.4 | 0.2 | 6.5 | 0.4 | 4.1 | < 0.1 | 4.8 | 0.0
Systemic Reactions
Myalgia | 35.3 | 1.6 | 35.2 | 1.8 | 27.4 | 1.9 | 31.2 | 1.9
Headache | 30.2 | 1.8 | 30.9 | 1.8 | 26.5 | 2.3 | 28.0 | 1.9
Malaise | 26.0 | 2.2 | 26.4 | 2.8 | 19.4 | 1.2 | 23.9 | 1.3
Fever [Any: ≥ 100.4°F (38.0°C); Grade 3: ≥ 102.1°F (39.0°C)] | 1.4 | 0.4 | 1.2 | 0.6 | 0.7 | 0.2 | 0.6 | 0.0

Among 296 participants who received Tdap and HPV concomitantly (without MenQuadfi) and 392 participants who received MenQuadfi concomitantly with Tdap and HPV, there were no notable differences in the rates of systemic solicited adverse reactions within 7 days following vaccination.

Dizziness within 30 minutes following vaccination was experienced by 1 (0.2%) participant who received MenQuadfi in Study 5 (NCT02199691) and 2 (0.2%) participants who received MenQuadfi in Study 6 (NCT02842853). Three participants in Study 5 experienced syncope within 30 minutes following vaccination: 1 (0.2%) participant who received Menveo, 1 (0.3%) participant who received MenQuadfi concomitantly with Tdap and HPV, and 1 (0.3%) participant who received Tdap and HPV concomitantly (without MenQuadfi). These events were non-serious and spontaneously resolved on the same day.

Adults 18 through 55 years of age

The safety of MenQuadfi in adults 18 through 55 years of age was evaluated in Study 6 (NCT02842853). The safety analysis set included 1495 participants who received MenQuadfi and 312 participants who received Menactra. Of the participants 18 years through 55 years of age who received MenQuadfi (N=1495), 65.2% were female. Among those with reported race and ethnicity, 73.3% were White, 21.0% were Black or African American, 2.2% were Asian, 3.5% were of other racial groups, and 20.0% were of Hispanic or Latino ethnicity. Mean age was 39.4 years at time of administration.

The rates and severity of the solicited adverse reactions that occurred within 7 days following MenQuadfi compared with Menactra are presented in Table 7.

Dizziness within 30 minutes following vaccination was experienced by 5 (0.3%) participants who received MenQuadfi and 1 (0.3%) participant who received Menactra. These events were non-serious and spontaneously resolved on the same day.

SAEs were reported by 1.6% of participants following MenQuadfi and 0.6% of participants following Menactra during the entire study period. No SAEs were determined to be vaccine related.

Table 7: Percentages of Solicited Injection-Site Reactions and Systemic Adverse Reactions within 7 Days after Vaccination with MenQuadfi or Menactra in Individuals 18 through 55 Years of Age (Study 6) [Clinical trial identifier NCT02842853]
 | MenQuadfi (N [N is the number of vaccinated participants with available data for the events listed] =1441–1460) % |  | Menactra (N=297–301) %
Adverse Reactions | Any | Grade 3 | Any | Grade 3
Local Reactions
Injection Site Pain [Grade 3: Prevents daily activity] | 41.9 | 1.9 | 35.0 | 1.3
Injection Site Erythema [Any: > 25 mm; Grade 3: > 100 mm] | 5.1 | 0.3 | 3.7 | 0.3
Injection Site Swelling | 4.3 | 0.2 | 3.4 | 0.3
Systemic Reactions
Myalgia | 35.6 | 3.6 | 31.2 | 2.3
Headache | 29.0 | 2.9 | 27.6 | 2.7
Malaise | 22.9 | 2.9 | 18.9 | 3.3
Fever [Any: ≥ 100.4°F (38.0°C); Grade 3: ≥ 102.1°F (39.0°C)] | 1.4 | 0.1 | 1.7 | 0.7

Adults 56 years of age and older

The safety of MenQuadfi in adults 56 years of age and older was evaluated in Study 7 (NCT02842866). The safety analysis set included 448 participants who received MenQuadfi intramuscularly and 453 participants who received a non-conjugate comparator meningococcal vaccine, Menomune® – A/C/Y/W-135 [Meningococcal Polysaccharide Vaccine, Groups A, C, Y, and W-135 Combined], subcutaneously. Of the participants 56 years of age and older who received MenQuadfi (N=448), 44.4% were 56 through 64 years of age, 55.6% were 65 years of age and older, 57.6% were female, 86.6% were White, 11.6% were Black or African American, 1.1% were Asian, 0.4% were of other racial groups and 7.8% were of Hispanic or Latino ethnicity. Mean age was 67.0 years at time of administration.

The rates and severity of the solicited adverse reactions that occurred within 7 days following MenQuadfi compared with Menomune in Study 7 (NCT02842866) are presented in Table 8.

SAEs were reported by 3.3% of participants following MenQuadfi and 3.3% of participants following Menomune during the entire study period. No SAEs were determined to be vaccine related.

Table 8: Percentages of Solicited Injection-Site Reactions and Systemic Adverse Reactions within 7 Days after Vaccination with MenQuadfi or Menomune in Individuals 56 Years of Age and Older (Study 7) [Clinical trial identifier NCT02842866]
 | MenQuadfi (N [N is the number of vaccinated participants with available data for the events listed] =436–443) % |  | Menomune [Menomune was given subcutaneously] (N=449–451) %
Adverse Reactions | Any | Grade 3 | Any | Grade 3
Local Reactions
Injection Site Pain [Grade 3: Prevents daily activity] | 25.5 | 0.7 | 9.6 | 0.7
Injection Site Erythema [Any: > 25 mm; Grade 3: > 100 mm] | 5.2 | 0.2 | 0.0 | 0.0
Injection Site Swelling | 4.5 | 0.0 | 0.0 | 0.0
Systemic Reactions
Myalgia | 21.9 | 1.6 | 15.3 | 1.3
Headache | 19.0 | 0.7 | 14.6 | 0.7
Malaise | 14.5 | 1.4 | 11.3 | 1.8
Fever [Any: ≥ 100.4°F (38.0°C); Grade 3: ≥ 102.1°F (39.0°C)] | 2.1 | 0.2 | 0.4 | 0.0

Booster Vaccination Following Priming with a Meningococcal Conjugate Vaccine; Vaccination Following a Prior Dose of a Meningococcal Polysaccharide Vaccine

Adolescents and adults 15 years of age and older

The safety of MenQuadfi in previously vaccinated adolescents and adults 15 years of age and older was evaluated in Study 8 (NCT02752906). All randomized participants had received a primary dose of either (Menveo or Menactra) 4 to 10 years previously. The safety analysis set included 402 participants who received a single booster dose of MenQuadfi (median age: 17.8 years) and 407 participants who received a single booster dose of Menactra (median age: 17.9 years). Of the participants who received MenQuadfi, 51.5% were female, 85.1% were White, 9.7% were Black, 2.7% were Asian and 2.2% were of other racial groups, and 15.7% were of Hispanic or Latino ethnicity.

The most commonly reported solicited adverse reactions (≥10%) within 7 days of MenQuadfi booster vaccination were injection site pain (44.7%) and headache (37.9%), myalgia (36.7%), and malaise (27.6%). The majority of solicited adverse reactions were Grade 1 or 2 and resolved within 3 days. Compared with recipients of a Menactra booster dose, recipients of a MenQuadfi booster dose had higher rates of injection site erythema (MenQuadfi 5.0%, Menactra 1.5%) and swelling (MenQuadfi 4.0%, Menactra 0.7%). Overall rates of solicited adverse reactions were comparable to those observed in unvaccinated adolescents and adults after a single MenQuadfi dose.

SAEs were reported by 1.2% of participants following MenQuadfi and 1.0% of participants following Menactra during the entire study period. No SAEs were determined to be vaccine related.

Adolescents and adults 13 through 26 years of age

The safety of MenQuadfi in previously vaccinated adolescents and adults 13 through 26 years of age was evaluated in Study 9 (NCT04084769). All randomized participants had received a primary dose of either MenQuadfi or Menveo 3–6 years previously. The safety analysis set included 370 participants who received a booster dose of MenQuadfi alone (median age: 15.0 years for participants primed with MenQuadfi and 16.0 years for participants primed with Menveo) and 185 participants who received MenQuadfi concomitantly with Trumenba® [Meningococcal Group B Vaccine] (N=93, median age: 15.0 years) or Bexsero® [Meningococcal Group B Vaccine] (N=92, median age: 15.0 years). Of the participants who received a booster dose of MenQuadfi, 47.2% were female, 88.1% were White, 8.2% were Black, 3.8% were of other racial groups, and 14.4% were of Hispanic or Latino ethnicity.

The rates and severity of the solicited adverse reactions that occurred within 7 days following a booster dose of MenQuadfi alone or concomitantly with Trumenba or Bexsero in Study 9 (NCT04084769) are presented in Table 9.

The majority of solicited reactions were Grade 1 or 2 and resolved within 3 days after vaccination.

There were no reported SAEs that were assessed as vaccine related.

Table 9: Percentages of Solicited Injection-Site Reactions and Systemic Adverse Reactions within 7 Days after Booster Vaccination with MenQuadfi Alone or MenQuadfi Concomitantly Administered with Trumenba or Bexsero in Individuals 13 Through 26 Years of Age Who Had Received a Primary Dose of MenQuadfi or Menveo 3–6 Years Previously (Study 9) [Clinical trial identifier NCT04084769]
 | MenQuadfi in MenQuadfi-primed (N=186) % |  | MenQuadfi in Menveo-primed (N=184) % |  | MenQuadfi and Trumenba in MenQuadfi-primed (N=93) % |  | MenQuadfi and Bexsero in MenQuadfi-primed (N=92) %
Adverse Reactions | Any | Grade 3 | Any | Grade 3 | Any | Grade 3 | Any | Grade 3
Local Reactions [Local reactions attributed to administration of MenQuadfi]
Injection Site Pain | 38.2 | 0.5 | 33.7 | 1.1 | 48.9 | 5.4 | 56.5 | 0
Injection Site Erythema | 6.5 | 0.5 | 5.4 | 0 | 1.1 | 0 | 6.5 | 1.1
Injection Site Swelling | 5.4 | 0 | 1.6 | 0 | 2.2 | 0 | 5.4 | 1.1
Systemic Reactions
Myalgia | 32.8 | 1.6 | 34.8 | 1.1 | 65.2 | 7.6 | 63.0 | 4.3
Headache | 36.0 | 1.1 | 34.8 | 1.6 | 42.4 | 4.3 | 39.1 | 2.2
Malaise | 26.9 | 2.2 | 25.5 | 2.2 | 39.1 | 5.4 | 40.2 | 3.3
Fever | 0 | 0 | 2.2 | 0.5 | 1.1 | 0 | 4.4 | 0
N: number of participants in the safety analysis set

Older adults ≥ 59 years of age

The safety of MenQuadfi in previously vaccinated older adults ≥ 59 years of age was evaluated in Study 10 (NCT04142242). All randomized participants had received a prior dose of either MenQuadfi (N=162) or Menomune (N=151) at a median interval of 3.34 and 3.35 years, respectively. The safety analysis set included 313 participants who received a dose of MenQuadfi (median age: 69.0 years for participants primed with MenQuadfi and 70.0 years for participants who received a prior dose of Menomune); 62.6% were female, 90.4% were White, 8.6% were Black, 0.3% were of other racial groups, and 10.5% were of Hispanic or Latino ethnicity.

The rates and severity of the solicited adverse reactions that occurred within 7 days following a dose of MenQuadfi in Study 10 (NCT04142242) are presented in Table 10.

The majority of solicited reactions were Grade 1 or 2 and resolved within 3 days after vaccination.

There were no reported SAEs that were assessed as vaccine related.

Table 10: Percentages of Solicited Injection-Site Reactions and Systemic Adverse Reactions within 7 Days after Vaccination with MenQuadfi in Individuals ≥ 59 Years of Age Who Had Received a Prior Dose of MenQuadfi or Menomune At Least 3 Years Previously (Study 10) [Clinical trial identifier NCT04142242]
 | MenQuadfi-primed (N=162) % |  | Prior dose of Menomune (N=151) %
Adverse Reactions | Any | Grade 3 | Any | Grade 3
Local Reactions
Injection Site Pain | 16.7 | 0 | 21.2 | 0.7
Injection Site Erythema | 3.7 | 0 | 7.3 | 0
Injection Site Swelling | 3.7 | 0 | 4.6 | 0
Systemic Reactions
Myalgia | 21.6 | 2.5 | 19.9 | 1.3
Headache | 18.5 | 0 | 13.9 | 0
Malaise | 13.6 | 1.9 | 14.6 | 2.6
Fever | 0.6 | 0 | 0 | 0
N: number of participants in the safety analysis set

6.2 Postmarketing Experience

The following adverse reactions have been identified during postmarketing use of MenQuadfi. Because these reactions are reported voluntarily from a population of uncertain size, it is not always possible to reliably estimate their frequency or establish a causal relationship to the vaccine.

Immune system disorder: Anaphylaxis and other forms of hypersensitivity.

Nervous system disorder: Febrile seizure, convulsion, syncope.

7 DRUG INTERACTIONS

7.1 Concomitant Administration with Other Vaccines

In a clinical trial in adolescents 10 through 17 years of age, MenQuadfi was administered concomitantly with Tdap and HPV [see Adverse Reactions (6) and Clinical Studies (14.3)].

Lower geometric mean antibody concentrations (GMCs) for antibodies to the pertussis antigens filamentous hemagglutinin (FHA), pertactin (PRN) and fimbriae (FIM) were observed when MenQuadfi was co-administered with Tdap and HPV, compared to concomitant administration of Tdap and HPV (without MenQuadfi) [see Clinical Studies (14.3)].

7.2 Immunosuppressive Treatments

Immunosuppressive therapies may reduce the immune response to MenQuadfi [see Warnings and Precautions (5)].

8 USE IN SPECIFIC POPULATIONS

8.1 Pregnancy

Pregnancy Exposure Registry

There is a pregnancy exposure registry that monitors pregnancy outcomes in women exposed to MenQuadfi during pregnancy. To enroll in or obtain information about the registry, call Sanofi Pasteur at 1-800-822-2463.

Risk Summary

All pregnancies have a risk of birth defect, loss, or other adverse outcomes. In the US general population, the estimated background risk of major birth defects and miscarriage in clinically recognized pregnancies is 2–4% and 15–20%, respectively.

There are no clinical studies of MenQuadfi in pregnant women. Available human data on MenQuadfi administered to pregnant women are insufficient to inform vaccine-associated risks in pregnancy.

A developmental toxicity study in female rabbits administered a full human dose (0.5 mL) prior to mating and during gestation period revealed no evidence of harm to the fetus due to MenQuadfi (see Animal Data).

Data

Animal Data

In a developmental toxicity study, female rabbits received a human dose of MenQuadfi by intramuscular injection on five occasions: 30 days and 10 days prior to mating, gestation days 6, 12 and 27. No adverse effects on pre-weaning development up to post-natal day 35 were observed. There were no vaccine-related fetal malformations or variations observed.

8.2 Lactation

Risk Summary

It is not known whether MenQuadfi is excreted in human milk. Data are not available to assess the effects of MenQuadfi on the breastfed infant or on milk production/excretion.

The developmental and health benefits of breastfeeding should be considered along with the mother's clinical need for MenQuadfi and any potential adverse effects on the breastfed child from MenQuadfi or from the underlying maternal condition. For preventive vaccines, the underlying maternal condition is susceptibility to disease prevented by the vaccine.

8.4 Pediatric Use

Safety and effectiveness of MenQuadfi have not been established in individuals younger than 6 weeks of age.

Safety and effectiveness of MenQuadfi have been established in individuals from 6 weeks through 17 years of age [see Adverse Reactions (6) and Clinical Studies (14)].

8.5 Geriatric Use

A total of 249 participants 65 years of age and older, including 71 participants 75 years of age or older, in Study 7 received one dose of MenQuadfi [see Adverse Reactions (6.1) and Clinical Studies (14.1)].

MenQuadfi recipients ≥ 65 years of age had lower GMTs and seroresponse rates for all serogroups compared to MenQuadfi recipients 56 through 64 years of age [see Clinical Studies (14.1)].

11 DESCRIPTION

MenQuadfi [Meningococcal (Groups A, C, Y, W) Conjugate Vaccine] is a sterile injection for intramuscular use that contains Neisseria meningitidis serogroup A, C, W, and Y capsular polysaccharide antigens that are individually conjugated to tetanus toxoid protein. N. meningitidis A, C, W, and Y strains are cultured on Mueller Hinton agar medium and grown in Watson Scherp medium. The polysaccharides are extracted from the N. meningitidis cells and purified by centrifugation, detergent precipitation, alcohol precipitation, solvent extraction, and diafiltration. To prepare the polysaccharides for conjugation, Serogroup A is activated with carbonyldiimidazole (CDI), derivatized with adipic acid dihydrazide (ADH), and purified by diafiltration. Serogroups C, W, and Y are depolymerized, activated with periodate, and purified by diafiltration.

Clostridium tetani is fermented in media to generate tetanus toxin, which is purified by ammonium sulfate precipitation to yield purified tetanus toxin (PTT) and detoxified with formaldehyde to yield purified tetanus protein (PTP). The PTP is then concentrated and filtered to yield concentrated tetanus protein (CTP). The activated/derivatized polysaccharides are covalently linked to tetanus toxoid and purified by chromatography and serial diafiltration. The four meningococcal components, present as individual serogroup-specific glycoconjugates, compose the final formulated vaccine.

MenQuadfi is manufactured as a sterile, clear, colorless solution. Each 0.5 mL dose of vaccine contains 10 microgram each of meningococcal A, C, W, and Y polysaccharide antigens conjugated to approximately 55 micrograms tetanus toxoid protein carrier; 3.35 mg sodium chloride (0.67%), and 1.23 mg sodium acetate (30 mM). Potency of MenQuadfi is determined by quantifying the amount of each polysaccharide antigen that is conjugated to tetanus toxoid protein and the amount of unconjugated polysaccharide present.

MenQuadfi does not contain a preservative. Each 0.5 mL dose may contain residual amounts of formaldehyde of less than 3 mcg/mL, by calculation.

The vial in which the vaccine components are contained is composed of USP Type I borosilicate glass. The vial stopper is a chlorobutyl synthetic polyisoprene blend stopper (not made with natural rubber latex).

12 CLINICAL PHARMACOLOGY

12.1 Mechanism of Action

Invasive meningococcal disease (IMD) is caused by the bacterium N. meningitidis, a gram-negative diplococcus found exclusively in humans. The presence of bactericidal anti-capsular meningococcal antibodies in serum has been associated with protection from IMD. MenQuadfi induces the production of bactericidal antibodies specific to the capsular polysaccharides of N. meningitidis serogroups A, C, W, and Y.

13 NONCLINICAL TOXICOLOGY

13.1 Carcinogenesis, Mutagenesis, Impairment of Fertility

MenQuadfi has not been evaluated for carcinogenic or mutagenic potential or for impairment of male fertility. MenQuadfi administered to female rabbits had no effects on fertility [see Use in Specific Populations (8.1)].

14 CLINICAL STUDIES

To infer effectiveness of MenQuadfi, the immunogenicity in persons 6 weeks of age and older was evaluated using a serogroup-specific serum bactericidal assay with exogenous human complement (hSBA). Serum was collected at baseline and 30 days post-vaccination to measure antibodies with hSBA. The hSBA geometric mean titers (GMTs) and proportion of participants who achieved hSBA seroresponse (defined below) were evaluated.

In all studies, the seroresponse rate for each serogroup was defined as: the proportion of participants with an hSBA

- pre-vaccination titer < 1:8 who achieved a post-vaccination titer ≥ 1:16, or
- pre-vaccination titer ≥ 1:8 who achieved a post-vaccination titer at least 4-fold greater than the pre-vaccination titer.

14.1 Primary Vaccination

Immunogenicity of a 4-dose series administered at 2, 4, 6, and 12 through 18 months of age

Study 1 evaluated the effectiveness of MenQuadfi, based on immune responses measured by hSBA, in comparison to Menveo following a 4-dose series (given at 2, 4, 6, and 12 through 15 months) when concomitantly administered with U.S. licensed vaccines [see Adverse Reactions (6.1)].

Immune non-inferiority was based on 1) percentage of participants with hSBA titers ≥ 1:8 following the 3rd dose of the 4-dose series and 2) seroresponse rates following completion of a 4-dose series at 2, 4, 6, and 12 through 15 months of age. Non-inferiority was met for both co-primary endpoints [the lower limit (LL) of the 2-sided 95% CI of the difference in rates (MenQuadfi – Menveo) was > -10%] for all four serogroups.

The percentage of participants with hSBA titers ≥ 1:8, hSBA seroresponse rate, and GMTs are presented in Table 11.

Table 11: Comparison of Bactericidal Antibody Responses to MenQuadfi and Menveo 30 Days after Vaccination at 2, 4, 6, and 12 through 15 Months (Study 1 [Clinical trial identifier NCT03537508. Pentacel was given at 2, 4, 6, and at 15 through 18 months of age; Prevnar 13 was given at 2, 4, 6, and 12 months of age; RotaTeq was given at 2, 4, and 6 months of age; Engerix-B was given at 2 and 6 months of age (first dose given 28 days prior to study); M-M-R II and Varivax was given at 12 months of age; and Havrix was given at 15 through 18 months of age.])
 | Post 3rd Dose [Per protocol analysis set 1 was used to evaluate antibody responses 30 days after the 3rd dose.] |  |  | Post 4th Dose [Per protocol analysis set 3 was used to evaluate antibody responses 30 days after the 4th dose. Participants ranged from 12 through 15 months of age at the time the fourth dose of MenQuadfi. Participants were 12 months of age at the time of the fourth dose of Menveo.]
Endpoint | MenQuadfi (95% CI) | Menveo (95% CI) | Percent difference MenQuadfi minus Menveo (95% CI) | MenQuadfi (95% CI) | Menveo (95% CI) | Percent difference MenQuadfi minus Menveo (95% CI)
A | N=682–852 | N=322–409 |  | N=501–642 | N=223–296
% ≥1:8 | 77.9 (75.0; 80.7) | 67.7 (63.0; 72.2) | 10.21 [Percentage of participants with hSBA titers ≥ 1:8 following the 3rd dose of the 4-dose series: Non-inferiority post-dose 3 will be demonstrated if the lower limit (LL) of the 2-sided 95% confidence interval (CI) of the difference in percentage participants with hSBA titers ≥ 1:8 30 days after the 3rd dose (MenQuadfi – Menveo) is > -10% for each meningococcal serogroup.] (4.98; 15.59) | 87.7 (84.9; 90.1) | 88.2 (83.9; 91.6)
% Participants achieving Seroresponse [Seroresponse rate for each serogroup was defined as the proportion of participants with an hSBA pre-vaccination titer (pre-dose 1) < 1:8 who achieved a post-vaccination titer ≥ 1:16, or pre-vaccination titer (pre-dose 1) ≥ 1:8 who achieved a post-vaccination titer at least 4-fold greater than the pre-vaccination titer (pre-dose 1). The proportion of participants with pre-dose 1 titers < 1:8 in the MenQuadfi or Menveo group, respectively, was 85.1% and 86.6% for serogroup A, 89.4% and 89.3% for serogroup C, 88.1% and 89.6% for serogroup W, and 84.4% and 85.4% for serogroup Y. The proportion of participants with pre-dose 1 titers ≥ 1:8 in the MenQuadfi or Menveo group, respectively, was 14.9% and 13.4% for serogroup A, 10.6% and 10.7% for serogroup C, 11.9% and 10.4% for serogroup W, and 15.6% and 14.6% for serogroup Y.] | 64.4 (60.6; 68.0) | 50.6 (45.0; 56.2) |  | 79.4 (75.6; 82.9) | 77.6 (71.5; 82.9) | 1.86 [Seroresponse rates following completion of a 4-dose series: Non-inferiority post-dose 4 will be demonstrated if the lower limit (LL) of the 2-sided 95% confidence interval (CI) of the difference in percentage of participant who achieve hSBA seroresponse 30 days after the 4th dose (MenQuadfi – Menveo) is > -10% for each meningococcal serogroup.] (-4.38; 8.64)
GMT | 25 (23; 28) | 15 (13; 18) |  | 67 (58; 78) | 57 (47; 70)
C | N=691–835 | N=338–421 |  | N=530–655 | N=238–300
% ≥1:8 | 99.0 (98.1; 99.6) | 91.2 (88.1; 93.7) | 7.83 (5.31; 10.96) | 99.4 (98.4; 99.8) | 93.3 (89.9; 95.9)
% Participants achieving Seroresponse | 96.4 (94.7; 97.6) | 82.8 (78.4; 86.7) |  | 97.0 (95.1; 98.3) | 88.2 (83.4; 92.0) | 8.75 (4.80; 13.60)
GMT | 391 (356; 428) | 53 (46; 61) |  | 678 (606; 758) | 91 (76; 109)
W | N=739–883 | N=369–438 |  | N=540–651 | N=250–305
% ≥1:8 | 98.6 (97.6; 99.3) | 92.9 (90.1; 95.1) | 5.72 (3.44; 8.57) | 99.4 (98.4; 99.8) | 99.0 (97.2; 99.8)
% Participants achieving Seroresponse | 92.8 (90.7; 94.6) | 85.6 (81.6; 89.1) |  | 97.6 (95.9; 98.7) | 96.4 (93.3; 98.3) | 1.19 (-1.18; 4.45)
GMT | 98 (91; 106) | 49 (43; 55) |  | 387 (352; 426) | 175 (149; 206)
Y | N=701–861 | N=347–423 |  | N=523–651 | N=233–295
% ≥1:8 | 98.3 (97.1; 99.0) | 91.7 (88.7; 94.2) | 6.53 (4.01; 9.62) | 99.1 (98.0; 99.7) | 98.6 (96.6; 99.6)
% Participants achieving Seroresponse | 88.7 (86.2; 91.0) | 81.8 (77.4; 85.8) |  | 96.4 (94.4; 97.8) | 92.3 (88.1; 95.4) | 4.09 (0.68; 8.44)
GMT | 88 (81; 96) | 41 (36; 46) |  | 296 (268; 327) | 186 (158; 219)
N: number of participants in per-protocol analysis set with valid serology results.
95% CI of the single proportion calculated from the exact binomial method

The percentage of participants with hSBA titers ≥ 1:8 prior to the 4th dose of MenQuadfi (given at 12 through 15 months of age, N=607–619) or Menveo (given at 12 months of age, N=282–288), respectively, was 62.8% and 46.5% for serogroup A, 93.1% and 30.6% for serogroup C, 97.1% and 61.5% for serogroup W, and 96.2% and 67.9% for serogroup Y. GMTs prior to the 4th dose of MenQuadfi or Menveo, respectively, were 11 and 7 for serogroup A, 61 and 4 for serogroup C, 58 and 9 for serogroup W, and 44 and 10 for serogroup Y.

In descriptive analyses, there were no notable differences in hSBA vaccine seroresponse rates observed with the administration of the 4th dose of MenQuadfi at 12 through 15 months of age or 15 through 18 months of age.

Immunogenicity of a 2-dose series administered between 6 and 23 months of age:

Immunogenicity of MenQuadfi compared to Menveo following a 2-dose series with the first dose administered at 6 through 7 months and the second dose administered at 12 through 13 months when concomitantly administered with U.S. licensed vaccines was evaluated in Study 3 [see Adverse Reactions (6.1)].

Immune non-inferiority was demonstrated based on the percentage of participants with hSBA titers ≥ 1:8 and hSBA seroresponse rates following administration of 2 doses [the lower limit of the 2-sided 95% CI of the difference in rates (MenQuadfi – Menveo) was > -10%] for all four serogroups.

The percentage of participants with hSBA titers ≥ 1:8, hSBA seroresponse rate, and GMTs are presented in Table 12.

Table 12: Comparison of Bactericidal Antibody Responses to MenQuadfi and Menveo 30 Days after Vaccination with a 2-dose Series (First Dose Administered at 6 through 7 Months of age and Second Dose Administered at 12 through 13 Months of Age) (Study 3 [Clinical trial identifier NCT03691610. At 6 months of age, Pediarix and a Hib vaccine (ActHIB or Hiberix or PedvaxHIB) OR Pentacel were given along with Prevnar 13, RotaTeq and Engerix-B. At 12 months of age, M-M-R II and Varivax were given.])
 | Post 2nd Dose
Endpoint | MenQuadfi (95% CI) | Menveo (95% CI) | Percent difference MenQuadfi minus Menveo (95% CI)
A | N=141–170 | N=123–158
% ≥1:8 | 95.3 (90.9; 97.9) | 93.0 (87.9; 96.5) | 2.26 [Percentage of participants with hSBA titers ≥ 1:8 following the 2nd dose: Non-inferiority post-dose 2 will be demonstrated if the lower limit (LL) of the 2-sided 95% confidence interval (CI) of the difference in percentage participants with hSBA titers ≥ 1:8 30 days after the 2nd dose (MenQuadfi – Menveo) is > -10% for each meningococcal serogroup.] (-3.01; 7.83)
% Participants achieving Seroresponse [Seroresponse rate for each serogroup is defined as the proportion of participants with an hSBA pre-vaccination titer (pre-dose 1) < 1:8 who achieved a post-vaccination titer ≥ 1:16, or pre-vaccination titer (pre-dose 1) ≥ 1:8 who achieved a post-vaccination titer at least 4-fold greater than the pre-vaccination titer (pre-dose 1). The proportion of participants with pre-dose 1 titers < 1:8 in the MenQuadfi or Menveo group, respectively, was 70.8% and 75.6% for serogroup A, 93.9% and 93.0% for serogroup C, 95.3% and 93.8% for serogroup W, and 91.3% and 93.8% for serogroup Y. The proportion of participants with pre-dose 1 titers ≥ 1:8 in the MenQuadfi or Menveo group, respectively, was 29.2% and 24.4% for serogroup A, 6.1% and 7.0% for serogroup C, 4.7% and 6.2% for serogroup W, and 8.7% and 6.2% for serogroup Y.] | 89.4 (83.1; 93.9) | 82.9 (75.1; 89.1) | 6.43 [Seroresponse rates following the 2nd dose: Non-inferiority post-dose 2 will be demonstrated if the lower limit (LL) of the 2-sided 95% confidence interval (CI) of the difference in percentage of participant who achieve hSBA seroresponse 30 days after the 2nd dose (MenQuadfi – Menveo) is > -10% for each meningococcal serogroup.] (-1.92; 15.08)
GMT | 184 (143; 237) | 119 (90.6; 157)
C | N=134–162 | N=126–160
% ≥1:8 | 100 (97.7; 100) | 98.1 (94.6; 99.6) | 1.88 (-0.75; 5.37)
% Participants achieving Seroresponse | 99.3 (95.9; 100) | 97.6 (93.2; 99.5) | 1.63 (-2.07; 6.06)
GMT | 1473 (1236; 1756) | 319 (263; 388)
W | N=143–171 | N=127–159
% ≥1:8 | 100 (97.9; 100) | 95.6 (91.1; 98.2) | 4.40 (1.25; 8.81)
% Participants achieving Seroresponse | 99.3 (96.2; 100) | 92.9 (86.9; 96.7) | 6.39 (1.81; 12.25)
GMT | 442 (367; 533) | 106 (83; 135)
Y | N=140–170 | N=128–160
% ≥1:8 | 100 (97.9; 100) | 97.5 (93.7; 99.3) | 2.50 (-0.18; 6.25)
% Participants achieving Seroresponse | 98.6 (94.9; 99.8) | 97.7 (93.3; 99.5) | 0.92 (-3.03; 5.36)
GMT | 423 (358; 499) | 133 (107; 166)
N: number of participants in per-protocol analysis set with valid serology results.
95% CI of the single proportion calculated from the exact binomial method

The percentage of participants with hSBA titers ≥ 1:8 prior to the 2nd dose of MenQuadfi (N=103–106) or Menveo (N=91–94), respectively, was 77.7% and 73.6% for serogroup A, 98.1% and 69.1% for serogroup C, 96.2% and 50.5% for serogroup W, and 96.2% and 54.8% for serogroup Y. GMTs prior to the 2nd dose of MenQuadfi or Menveo, respectively, were 20 and 15 for serogroup A, 150 and 13 for serogroup C, 47 and 6 for serogroup W, and 46 and 7 for serogroup Y.

The immunogenicity of MenQuadfi compared to Menactra following a 2-dose series with the first dose administered at 17 through 19 months and the second dose at 20 through 23 months of age was also descriptively evaluated in Study 3. The seroresponse rates following the second dose of MenQuadfi (N=59–61) or Menactra (N=58–65), respectively, at 20 through 23 months of age were 72.9% and 46.6% for serogroup A, 100% and 93.2% for serogroup C, 100% and 76.3% for serogroup W, and 100% and 88.1% for serogroup Y. The percentage of participants with hSBA titers ≥ 1:8 following the second dose of MenQuadfi or Menactra, respectively, were 88.5% and 62.5% for serogroup A, 100% and 98.5% for serogroup C, 100% and 84.6% for serogroup W, and 100% and 92.3% for serogroup Y. hSBA GMTs following the second dose of MenQuadfi or Menactra, respectively, were 45 and 13 for serogroup A, 1727 and 59 for serogroup C, 202 and 25 for serogroup W, and 284 and 46 for serogroup Y.

Immunogenicity in Children 2 through 9 Years of Age

Immunogenicity of MenQuadfi compared to Menveo in participants 2 through 9 years of age was evaluated in Study 4 (NCT03077438). The hSBA seroresponse rate and GMTs are presented in Table 13.

Immune non-inferiority, based on seroresponse rates, was demonstrated for MenQuadfi as compared to Menveo for all four serogroups.

Table 13: Comparison of Bactericidal Antibody Responses to MenQuadfi and Menveo 30 Days after Vaccination of Participants 2 through 9 Years of Age (Study 4) [Clinical trial identifier NCT03077438]
Endpoint [Seroresponse rate (primary endpoint) for each serogroup: the proportion of participants with an hSBA pre-vaccination titer < 1:8 who achieved a post-vaccination titer ≥ 1:16, or pre-vaccination titer ≥ 1:8 who achieved a post-vaccination titer at least 4-fold greater than the pre-vaccination titer.] | MenQuadfi (95% CI) | Menveo (95% CI) | Percent difference MenQuadfi minus Menveo [Overall non-inferiority would be demonstrated if the lower limit of the 2-sided 95% CI is > -10% for all four serogroups.] (95% CI)
A | N=455–456 | N=458
% Participants achieving Seroresponse | 55.4 (50.7; 60.0) | 47.8 (43.2; 52.5) | 7.6 (1.1, 14.0)
GMT | 25 (22; 28) | 23 (20; 26)
C | N=458 | N=458–459
% Participants achieving Seroresponse | 95.2 (92.8; 97.0) | 47.8 (43.2; 52.5) | 47.4 (42.2, 52.2)
GMT | 238 (209; 270) | 17.0 (14; 20)
W | N=458 | N=459
% Participants achieving Seroresponse | 78.8 (74.8; 82.5) | 64.1 (59.5; 68.4) | 14.8 (8.9, 20.5)
GMT | 38 (34; 42) | 26 (23; 30)
Y | N=458 | N=459
% Participants achieving Seroresponse | 91.5 (88.5; 93.9) | 79.3 (75.3; 82.9) | 12.2 (7.7, 16.7)
GMT | 69 (61; 77) | 44 (38; 50)
N: number of participants in per-protocol analysis set with valid serology results.
95% CI of the single proportion calculated from the exact binomial method.
95% CI of the difference calculated from the Wilson Score method without continuity correction.

Immunogenicity in Adolescents 10 through 17 Years of Age

Immunogenicity of MenQuadfi compared to Menveo in participants 10 through 17 years of age was evaluated in Study 5 (NCT02199691). Study 5 was conducted in healthy meningococcal vaccine naïve participants and evaluated seroresponse rates following administration with either MenQuadfi alone, Menveo alone, MenQuadfi co-administered with Tdap, and HPV, or Tdap and HPV alone. The hSBA seroresponse rate and GMTs for Study 5 are presented in Table 13.

Immune non-inferiority, based on seroresponse, was demonstrated for MenQuadfi as compared to Menveo for all four serogroups.

Study 5 (NCT02199691) was conducted in healthy meningococcal vaccine naïve male and female participants and evaluated seroresponses following administration with either MenQuadfi alone; Menveo alone; MenQuadfi co-administered with Tdap, and HPV; or Tdap and HPV alone. The hSBA seroresponse rate and GMTs for the MenQuadfi alone and Menveo alone groups are presented in Table 14.

Table 14: Comparison of Bactericidal Antibody Responses to MenQuadfi and Menveo 30 Days after Vaccination of Participants 10 through 17 Years of Age (Study 5) [Clinical trial identifier NCT02199691]
Endpoint [Seroresponse rate (primary endpoint) for each serogroup: the proportion of participants with an hSBA pre-vaccination titer < 1:8 who achieved a post-vaccination titer ≥ 1:16, or pre-vaccination titer ≥ 1:8 who achieved a post-vaccination titer at least 4-fold greater than the pre-vaccination titer.] | MenQuadfi (95% CI) | Menveo (95% CI) | Percent difference MenQuadfi minus Menveo [Overall non-inferiority would be demonstrated if the lower limit of the 2-sided 95% CI is > -10% for all four serogroups.] (95% CI)
A | N=463 | N=464
% Participants achieving Seroresponse | 70.2 (65.8; 74.3) | 60.3 (55.7; 64.8) | 9.8 (3.7;15.9)
GMT | 44 (39; 50) | 35 (30; 41)
C | N=462 | N=463
% Participants achieving Seroresponse | 96.1 (93.9, 97.7) | 61.6 (57.0, 66.0) | 34.5 (29.7; 39.3)
GMT | 387 (329; 456) | 51 (41; 64)
W | N=463 | N=464
% Participants achieving Seroresponse | 84.2 (80.6; 87.4) | 56.0 (51.4; 60.6) | 28.2 (22.5; 33.7)
GMT | 87 (78; 97) | 36 (32; 41)
Y | N=462–463 | N=464
% Participants achieving Seroresponse | 91.1 (88.2; 93.6) | 66.8 (62.3;71.1) | 24.3 (19.2; 29.3)
GMT | 76 (66; 87) | 28 (24; 32)
N: number of participants in per-protocol analysis set with valid serology results.
95% CI of the single proportion calculated from the exact binomial method.
95% CI of the difference calculated from the Wilson Score method without continuity correction.

Study 6 evaluated the immunogenicity of MenQuadfi (N=1097–1098) compared to Menactra (N=300) in healthy meningococcal-naïve participants 10 through 17 years of age. Seroresponse rates for MenQuadfi were noninferior to those of Menactra for all serogroups based on the same non-inferiority criteria defined for Study 5.

Immunogenicity in Adults 18 through 55 Years of Age

Immunogenicity of MenQuadfi compared to Menactra in participants 18 through 55 years of age was evaluated in Study 6 (NCT02842853). The hSBA seroresponse rate and GMTs are presented in Table 15.

Immune non-inferiority, based on seroresponse rates, was demonstrated for MenQuadfi as compared to Menactra for all four serogroups.

Table 15: Comparison of Bactericidal Antibody Responses to MenQuadfi and Menactra 30 Days after Vaccination of Participants 18 through 55 Years of Age (Study 6) [Clinical trial identifier NCT02842853]
Endpoint [Seroresponse rate (primary endpoint) for each serogroup: the proportion of participants with an hSBA pre-vaccination titer < 1:8 who achieved a post-vaccination titer ≥ 1:16, or pre-vaccination titer ≥ 1:8 who achieved a post-vaccination titer at least 4-fold greater than the pre-vaccination titer.] | MenQuadfi (95% CI) | Menactra (95% CI) | Percent difference MenQuadfi minus Menactra [The overall non-inferiority would be demonstrated if the lower limit of the 2-sided 95% CI is > -10% for all four serogroups.] (95% CI)
A | N=1406–1408 | N=293
% Participants achieving Seroresponse | 73.5 (71.2; 75.8) | 53.9 (48.0; 59.7) | 19.6 (13.5; 25.8)
GMT | 106 (97; 117) | 52 (43; 64)
C | N=1406–1408 | N=293
% Participants achieving Seroresponse | 83.4 (81.4; 85.3) | 42.3 (36.6; 48.2) | 41.1 (35.0; 46.9)
GMT | 234 (210; 261) | 37 (29; 49)
W | N=1408–1410 | N=293
% Participants achieving Seroresponse | 77.0 (74.7; 79.2) | 50.2 (44.3; 56.0) | 26.8 (20.7; 32.9)
GMT | 76 (69; 83) | 33 (26; 42)
Y | N=1408–1410 | N=293
% Participants achieving Seroresponse | 88.1 (86.3; 89.8) | 60.8 (54.9; 66.4) | 27.4 (21.7; 33.3)
GMT | 219 (200; 239) | 55 (42; 70)
N: number of participants in per-protocol analysis set with valid serology results.
95% CI of the single proportion calculated from the exact binomial method.
95% CI of the difference calculated from the Wilson Score method without continuity correction.

Immunogenicity in Adults 56 Years of Age and Older

Immunogenicity of MenQuadfi compared to Menomune in participants 56 years and older was evaluated in Study 7 (NCT02842866).

Enrollment was stratified by age category: 56 through 64 years of age (44.3%), 65 through 74 years of age (39.7%), and 75 years of age and older (15.9%). The overall mean age of participants who received MenQuadfi was 66.9 years; range: 56 through 89.8 years of age. The mean age for participants in the 56 through 64 years age stratum who received MenQuadfi was 60.4 years, the mean age for participants ≥ 65 years age stratum who received MenQuadfi was 72.2 years.

The hSBA seroresponse rate and GMTs are presented in Table 16.

Immune non-inferiority, based on seroresponse rates, was demonstrated for MenQuadfi as compared to Menomune for all four serogroups.

Table 16: Comparison of Bactericidal Antibody Responses to MenQuadfi and Menomune in Naïve Older Adults and Elderly 30 Days after Vaccination (Study 7) [Clinical trial identifier NCT02842866]
Endpoint [Seroresponse rate (primary endpoint) for each serogroup: the proportion of participants with an hSBA pre-vaccination titer < 1:8 who achieved a post-vaccination titer ≥ 1:16, or pre-vaccination titer ≥ 1:8 who achieved a post-vaccination titer at least 4-fold greater than the pre-vaccination titer.] | MenQuadfi (95% CI) | Menomune (95% CI) | Percent difference MenQuadfi minus Menomune [The overall non-inferiority would be demonstrated if the lower limit of the 2-sided 95% CI is > -10% for all four serogroups.] (95% CI)
A | N=433 | N=431
% Participants achieving Seroresponse | 58.2 (53.4; 62.9) | 42.5 (37.7; 47.3) | 15.7 (9.08; 22.2)
GMT | 55 (47; 65) | 31 (27; 37)
C | N=433 | N=431
% Participants achieving Seroresponse | 77.1 (72.9; 81.0) | 49.7 (44.8; 54.5) | 27.5 (21.2; 33.5)
GMT | 101 (84; 123) | 25 (21; 30)
W | N=433 | N=431
% Participants achieving Seroresponse | 62.6 (57.8; 67.2) | 44.8 (40.0; 49.6) | 17.8 (11.2; 24.2)
GMT | 28 (24; 33) | 15 (13; 18)
Y | N=433 | N=431
% Participants achieving Seroresponse | 74.4 (70.0; 78.4) | 43.4 (38.7; 48.2) | 31.0 (24.6; 37.0)
GMT | 69 (59; 81) | 21 (17; 25)
N: number of participants in per-protocol analysis set with valid serology results.
95% CI of the single proportion calculated from the exact binomial method.
95% CI of the difference calculated from the Wilson Score method without continuity correction.

14.2 Booster Vaccination Following Priming with a Meningococcal Conjugate Vaccine; Vaccination Following a Prior Dose of a Meningococcal Polysaccharide Vaccine

Immunogenicity in Adolescents and Adults at least 15 Years of Age and Older

Immunogenicity of a booster dose of MenQuadfi compared to a booster dose of Menactra was evaluated in Study 8 (NCT02752906). The study-enrolled participants 15 years of age and older who had received a primary dose of Menveo or Menactra 4 to 10 years previously.

Immune non-inferiority, based on seroresponse rates, was demonstrated for MenQuadfi as compared to Menactra for all four serogroups.

For a description of study design and number of participants, see section 6.1 Booster Vaccination Following Priming with a Meningococcal Conjugate Vaccine; Vaccination Following a Prior Dose of a Meningococcal Polysaccharide Vaccine. The primary immunogenicity endpoint was hSBA seroresponse to each serogroup 30 days following booster vaccination with MenQuadfi or Menactra given to participants who received a prior dose of Menveo or Menactra 4 to 10 years ago. The other endpoints included the proportions of participants with post-vaccination hSBA ≥1:8 and the hSBA GMTs for each serogroup. These endpoints were also evaluated at 6 days post vaccination in a subset.

Seroresponse rates at Day 30 following booster vaccination with MenQuadfi were 92.2% for serogroup A, 97.1% for serogroup C, 98.2% for serogroup W, and 97.4% for serogroup Y, as compared to 87.1% for serogroup A, 91.8% for serogroup C, 90.7% for serogroup W, and 95.6% for serogroup Y, following booster vaccination with Menactra. At Day 6, following booster vaccination with MenQuadfi, seroresponse rates were 72.7%, 83.6%, 94.5%, and 90.9% for serogroups A, C, W, and Y, respectively.

The hSBA GMTs were 173, 334, 499, and 302 for serogroups A, C, W, and Y at Day 6, and 497, 2618, 1747, and 2070, respectively, for the 4 serogroups at Day 30 following booster dose of MenQuadfi.

Overall, similar seroresponse rates were observed for those participants who received booster vaccination with Menactra.

Immunogenicity in Adolescents and Adults 13 through 26 Years of Age

Immunogenicity of a booster dose of MenQuadfi was evaluated in Study 9 (NCT04084769). The study enrolled participants 13 through 26 years of age who had received a primary dose of MenQuadfi or Menveo 3–6 years previously in Study 5 or Study 6.

For a description of study design and number of participants, see section 6.1 Booster Vaccination Following Priming with a Meningococcal Conjugate Vaccine; Vaccination Following a Prior Dose of a Meningococcal Polysaccharide Vaccine. The primary immunogenicity endpoints were hSBA seroresponse to each serogroup 30 days following a booster vaccination with MenQuadfi given to participants who received a prior dose of MenQuadfi or Menveo 3–6 years previously (Table 17). The other endpoints included hSBA GMTs for each serogroup. These endpoints were also evaluated at 6 days post vaccination in a subset (Per-Protocol Analysis Set 1).

Table 17: Comparison of hSBA Seroresponse Rates 30 Days Following Booster Vaccination with MenQuadfi in Participants 13 through 26 Years of Age Primed with MenQuadfi or Menveo 3–6 Years Previously (Study 9) [Clinical trial identifier NCT04084769]
[Seroresponse rate (primary endpoint) for each serogroup: the proportion of participants with an hSBA pre vaccination titer < 1:8 who achieved a post-vaccination titer ≥ 1:16, or pre-vaccination titer ≥ 1:8 who achieved a post-vaccination titer at least 4-fold greater than the pre-vaccination titer. Sufficiency of hSBA seroresponse after MenQuadfi vaccination was demonstrated if the lower limit of the 2-sided 95% CI was >75%.] Endpoint by Serogroup | MenQuadfi-primed (95% CI) N=174 | Menveo-primed (95% CI) N=176
A
% Participants achieving Seroresponse | 94.8 (90.4; 97.6) | 93.2 (88.4; 96.4)
C
% Participants achieving Seroresponse | 97.1 (93.4; 99.1) | 98.9 (96.0; 99.9)
W
% Participants achieving Seroresponse | 97.7 (94.2; 99.4) | 98.9 (96.0; 99.9)
Y
% Participants achieving Seroresponse | 98.9 (95.9; 99.9) | 100 (97.9; 100)
N: number of participants in Per-Protocol Analysis Set 2 (D30) with valid serology results.

Seroresponse rates at Day 6 following booster dose with MenQuadfi were 82.6%, 89.1%, 97.8%, and 95.7% for serogroups A, C, W, and Y, respectively, in MenQuadfi-primed participants (N=46) and 77.8%, 93.3%, 88.9%, and 91.1% for serogroups A, C, W, and Y, respectively, in Menveo-primed participants (N=45).

Following a booster dose of MenQuadfi, the hSBA GMTs at Day 6 were 289, 3799, 1928, and 1658 for MenQuadfi-primed participants (N=46) and 161, 919, 708, and 800 for Menveo-primed participants (N=45) for serogroups A, C, W, and Y, respectively. At D30, the hSBA GMTs were 502, 3708, 2290, and 2308 for MenQuadfi-primed participants (N=174) and 399, 2533, 2574, and 3036 for Menveo-primed participants (N=176).

Prior to booster vaccination, the percentage of participants with hSBA titers ≥1:8 for serogroups A, C, W, and Y were 71.3%, 87.9%, 86.2%, and 79.9% for those who received a prior dose of MenQuadfi 3–6 years earlier (N=174), and 71.0%, 50.6%, 77.8%, and 52.8% for those who received a prior dose of Menveo 3–6 years earlier (N=176).

Immunogenicity in Older Adults ≥ 59 Years of Age

Immunogenicity of a dose of MenQuadfi was evaluated in Study 10 (NCT04142242). The study enrolled participants ≥ 59 years of age who had received a prior dose of MenQuadfi or Menomune at least 3 years previously in Study 7 (NCT02842866).

For a description of study design and number of participants, see section 6.1 Booster Vaccination Following Priming with a Meningococcal Conjugate Vaccine; Vaccination Following a Prior Dose of a Meningococcal Polysaccharide Vaccine. The primary immunogenicity endpoint was hSBA seroresponse to each serogroup 30 days following vaccination with MenQuadfi in participants who had received a prior dose of Menomune 3 years previously. Additionally, hSBA seroresponse 30 days following vaccination with MenQuadfi in MenQuadfi-primed participants was also assessed (Table 18). The other endpoints included the hSBA GMTs for each serogroup. These endpoints were also evaluated at 6 days post vaccination in a subset (Per-Protocol Analysis Set 2).

Table 18: Comparison of hSBA Seroresponse Rates 30 Days Following Vaccination with MenQuadfi in Participants ≥ 59 Years of Age Primed with MenQuadfi or Received a Prior Dose of Menomune At Least 3 Years Previously (Study 10) [Clinical trial identifier NCT04142242]
[Seroresponse rate (primary endpoint) for each serogroup: the proportion of participants with an hSBA pre vaccination titer < 1:8 who achieved a post-vaccination titer ≥ 1:16, or pre-vaccination titer ≥ 1:8 who achieved a post-vaccination titer at least 4-fold greater than the pre-vaccination titer. Sufficiency of hSBA seroresponse after MenQuadfi vaccination was demonstrated if the lower limit of the 2-sided 95% CI was >40%.] Endpoint by Serogroup | MenQuadfi-primed (95% CI) | Prior dose of Menomune (95% CI)
A | N=145 | N=130
% Participants achieving Seroresponse | 79.3 (71.8; 85.6) | 60.8 (51.8; 69.2)
C
% Participants achieving Seroresponse | 93.1 (87.7; 96.6) | 55.0 (46.0; 63.8)
W
% Participants achieving Seroresponse | 90.3 (84.3; 94.6) | 49.2 (40.4; 58.1)
Y
% Participants achieving Seroresponse | 92.4 (86.8; 96.2) | 49.2 (40.4; 58.1)
N: number of participants in Per-Protocol Analysis Set 1 (D30) with valid serology results

Seroresponse rates at Day 6 following vaccination with MenQuadfi were 36.2%, 77.6%, 70.7%, and 72.4% for serogroups A, C, W, and Y, respectively, in MenQuadfi-primed participants (N=58) and 8.1%, 8.1%, 6.5%, and 8.1% for serogroups A, C, W, and Y, respectively, in participants who received a prior dose of Menomune (N=62).

Following vaccination with MenQuadfi, the hSBA GMTs at Day 6 were 44, 206, 118, and 151 for MenQuadfi-primed participants (N=58) and 13, 11, 10, and 11 for participants who received a prior dose of Menomune (N=62) for serogroups A, C, W, and Y, respectively. At D30, the hSBA GMTs were 162, 638, 419, and 566 for MenQuadfi-primed participants (N=145) and 57, 56, 31, and 41 for participants who received a prior dose of Menomune (N=130).

Prior to MenQuadfi vaccination, the percentage of participants with hSBA titers ≥1:8 for serogroups A, C, W, and Y were 64.8%, 73.8%, 66.9%, and 72.4% for those who received a prior dose of MenQuadfi at least 3 years earlier (N=145), and 65.4%, 49.2%, 40.0%, and 41.5% for those who received a prior dose of Menomune at least 3 years earlier (N=130).

14.3 Immunogenicity of Concomitantly Administered Vaccines

Study 1 evaluated the immunogenicity of DTaP-IPV/Hib, PCV13, HepB, MMR and varicella vaccine when given concomitantly with MenQuadfi compared to Menveo [see Adverse Reactions (6.1)]. The immune responses to DTaP-IPV/Hib, PCV13, and HepB were evaluated 1 month following Dose 3 of each of these vaccines. The immune responses to PCV13 and DTaP-IPV/Hib were evaluated 1 month after Dose 4 of each of these vaccines. The immune responses to MMR and varicella vaccine were evaluated 1 month after vaccination. In addition, the immune response to DTaP-IPV/Hib when given concomitantly with MenQuadfi at 15 through 18 months of age was compared to DTaP-IPV/Hib given alone at 15 through 18 months.

No interference in immune responses to these vaccines was observed when they were given concomitantly with MenQuadfi.

Concomitant administration of MenQuadfi with Tdap and HPV in adolescents 10 through 17 years was evaluated in Study 5 (NCT02199691). In this randomized study, 503 participants received MenQuadfi alone, 392 received MenQuadfi coadministered with Tdap and HPV, 296 received Tdap and HPV alone. A fourth group received Menveo alone (N=501).

No evidence of interference in hSBA seroresponse rates was observed when MenQuadfi was coadministered with Tdap and HPV. Antibody responses to HPV, and to the tetanus and diphtheria antigens were similar when Tdap and HPV were administered with and without MenQuadfi. Anti-pertussis GMC responses were non-inferior for the pertussis toxoid antigen, but did not meet non-inferiority for the FHA, PRN, and FIM antigens. The clinical relevance of the diminished responses to the pertussis antigens is unknown.

16 HOW SUPPLIED/STORAGE AND HANDLING

MenQuadfi is supplied in a single-dose vial (NDC 49281-590-58):

in packages of 1 vial (NDC 49281-590-01);

in packages of 5 vials (NDC 49281-590-05);

in packages of 10 vials (NDC 49281-590-10).

Not all pack sizes may be marketed.

The vial stopper is not made with natural rubber latex.

STORAGE AND HANDLING

Store at 2°C to 8°C (35°F to 46°F). Do not freeze. Do not use vaccine that has been frozen. Do not use after expiration date.

17 PATIENT COUNSELING INFORMATION

Vaccine Information Statements are required by the National Childhood Vaccine Injury Act of 1986 to be given prior to immunization to the patient, parent, or guardian. These materials are available free of charge at the Centers for Disease Control and Prevention (CDC) website (www.cdc.gov/vaccines). Inform the patients, parents or guardians about:

- Potential benefits and risks of immunization with MenQuadfi.
- Potential for adverse reactions that have been temporally associated with administration of MenQuadfi or other vaccines containing similar components.
- Reporting any adverse reactions to their healthcare provider.
- The Sanofi Pasteur Inc. Pregnancy Registry, as appropriate [see Pregnancy (8.1)].

MenQuadfi is a registered trademark of Sanofi Pasteur Inc.
Menactra, Adacel and Menomune are registered trademarks of Sanofi, its affiliates and/or its subsidiaries.
The other brands listed are trademarks owned by or licensed to their respective owners and are not owned by or licensed to Sanofi, its affiliates and/or its subsidiaries.

Manufactured by:
Sanofi Pasteur Inc.
Swiftwater PA 18370 USA

© 2025, Sanofi Pasteur Inc. - All rights reserved

R10-0525

PRINCIPAL DISPLAY PANEL - 0.5 mL Vial Label

NDC 49281-590-58

Meningococcal
(Groups A, C, Y, W)
Conjugate Vaccine
MenQuadfi®
Rx only
single-dose (0.5 mL)
Mfd by: Sanofi Pasteur Inc.

910266

Lot
EXP

PRINCIPAL DISPLAY PANEL - 0.5 mL Vial Carton

NDC 49281-590-10

MenACWY

Meningococcal (Groups A, C, Y, W)
Conjugate Vaccine

MenQuadfi®

Rx only

For intramuscular use.
For 6 weeks of age and older

10 single-dose vials
A dose is 0.5 mL

sanofi